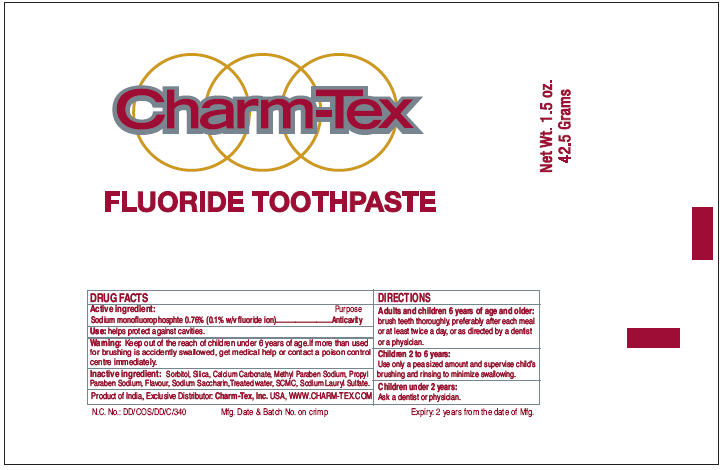 DRUG LABEL: Charm Tex
NDC: 40057-1000 | Form: PASTE, DENTIFRICE
Manufacturer: Charm Tex, Inc.
Category: otc | Type: HUMAN OTC DRUG LABEL
Date: 20111229

ACTIVE INGREDIENTS: Sodium monofluorophosphate 0.76 g/100 g
INACTIVE INGREDIENTS: Calcium Carbonate 42 g/100 g; Sorbitol; Silicon Dioxide; Sodium Lauryl Sulfate; Carboxymethylcellulose Sodium; Saccharin Sodium Dihydrate; Methylparaben Sodium; Propylparaben Sodium

Charm-Tex
FLUORIDE TOOTHPASTE

DRUG FACTS

Active ingredient

Sodium monofluorophosphte 0.76% (0.1% w/v fluoride ion)

Purpose

Anticavity

Use

helps protect against cavities.

Warning

KEEP OUT OF REACH OF CHILDREN

Keep out of the reach of children under 6 years of age.

WHEN USING

If more than used for brushing is accidently swallowed, get medical help or contact a poison control centre immediately.

Inactive ingredient

Sorbitol, Silica, Calcium Carbonate, Methyl Paraben Sodium, Propyl Paraben Sodium, Flavour, Sodium Saccharin,Treated water, SCMC, Sodium Lauryl Sulfate.

Directions

Adults and children 6 years of age and older

brush teeth thoroughly, preferably after each meal or at least twice a day, or as directed by a dentist or a physician.

Children 2 to 6 years

Use only a pea sized amount and supervise child's brushing and rinsing to minimize swallowing.

Children under 2 years

Ask a dentist or physician.

Exclusive Distributor: Charm-Tex, Inc. USA

PRINCIPAL DISPLAY PANEL - 42.5 Grams Tube Label

Charm-Tex

FLUORIDE TOOTHPASTE

Net Wt. 1.5 oz.
42.5 Grams